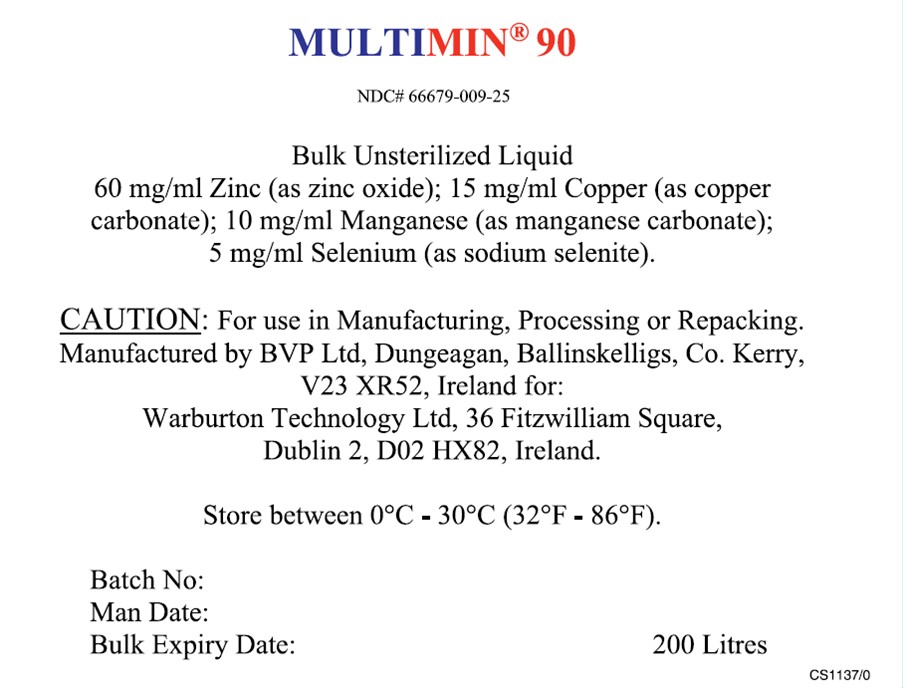 DRUG LABEL: Multimin 90
NDC: 66679-009 | Form: SOLUTION
Manufacturer: Warburton Technology Limited
Category: other | Type: BULK INGREDIENT - ANIMAL DRUG
Date: 20251013

ACTIVE INGREDIENTS: ZINC OXIDE 60 g/1 L; MANGANESE CARBONATE 10 g/1 L; SODIUM SELENITE 5 g/1 L; CUPRIC CARBONATE 15 g/1 L
INACTIVE INGREDIENTS: EDETIC ACID; BENZYL ALCOHOL; WATER; SODIUM HYDROXIDE

Multimin 90

WARNINGS AND PRECAUTIONS

For use in Manufacturing, Processing or Repacking

STORAGE AND HANDLING

Store between 0°C - 30°C (32°F - 86°F).

Package label.principal display panel

MULTIMIN 90
NDC# 66679-009-25
Bulk Unsterilized Liquid
60 mg/ml Zinc (as zinc oxide); 15 mg/ml Copper (as copper carbonate) 10 mg/ml Manganee (as manganese carbonate); 5mg/ml Selenium (as sodium selenite).
CAUTION: For use in Manufacturing, Processing or Repacking
Manufactured by BVP Ltd, Dungeagan, Ballinskelligs, Co. Kerry, V23 XR52, Ireland for:
Warburton Technology Ltd, 36 Fitzwilliam Square, Dublin 2, D02 HX82, Ireland.
Store between 0°C - 30°C (32°F - 86°F).
Batch No:
Man Date:

Bulk Expiry Date: 200 Litres